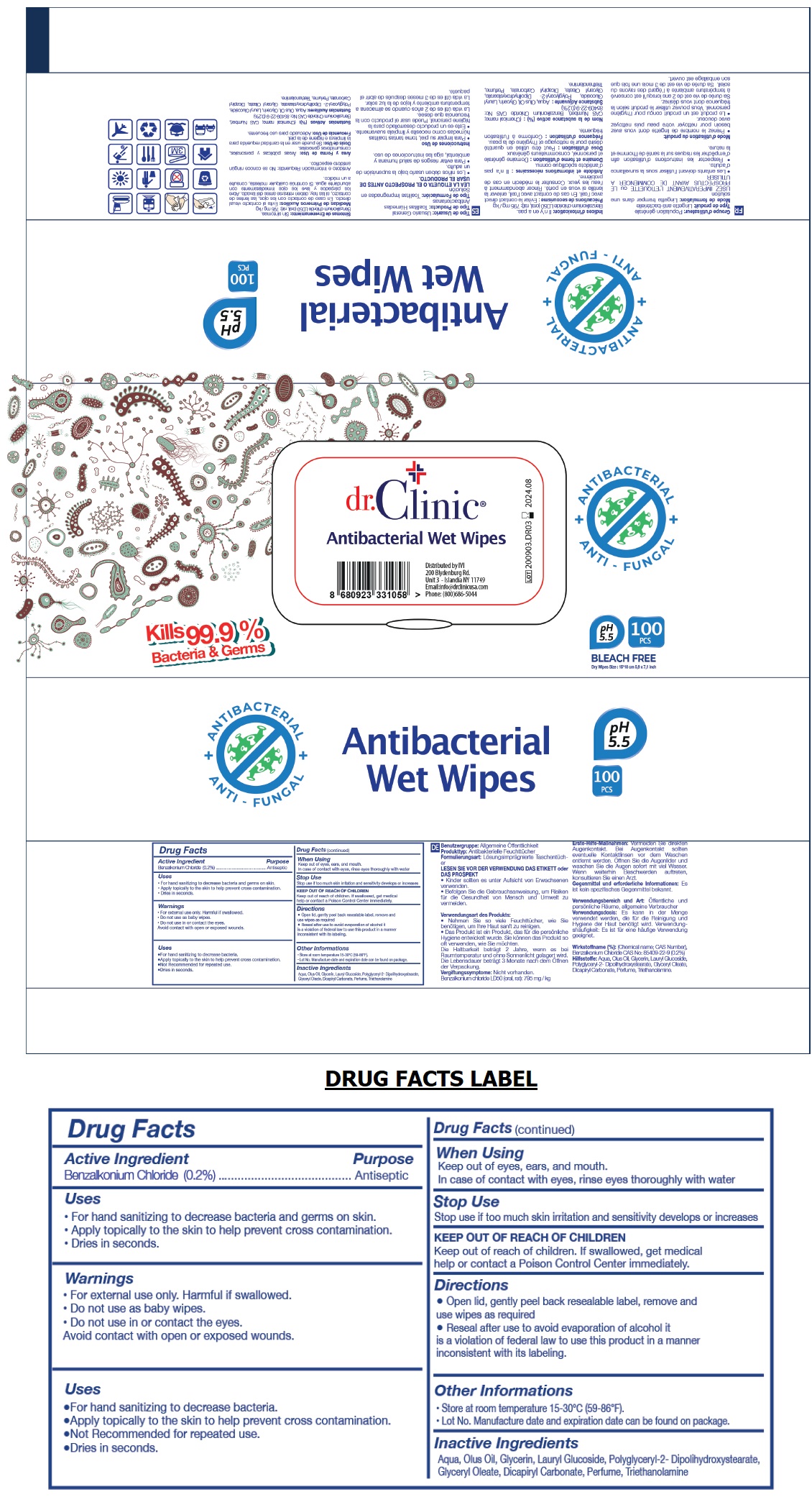 DRUG LABEL: DR CLINIC ANTIBACTERIAL WET WIPES
NDC: 76725-013 | Form: CLOTH
Manufacturer: MAKYAJ KOZMETIK INSAAT SANAYI VE TICARET LIMITED SIRKETI
Category: otc | Type: HUMAN OTC DRUG LABEL
Date: 20200910

ACTIVE INGREDIENTS: BENZALKONIUM CHLORIDE 0.2 g/100 g
INACTIVE INGREDIENTS: WATER; CORN OIL; GLYCERIN; LAURYL GLUCOSIDE; POLYGLYCERYL-2 DIPOLYHYDROXYSTEARATE; GLYCERYL OLEATE; DICAPRYLYL CARBONATE; TROLAMINE

dr. Clinic® Antibacterial Wet Wipes

Active Ingredient

Benzalkonium Chloride (0.2%)

Purpose

Antiseptic

Uses

• For hand sanitizing to decrease bacteria and germs on skin.

• Apply topically to the skin to help prevent cross contamination.

• Not Recommended for repeated use.

• Dries in seconds.

Warnings

• For external use only. Harmful if swallowed.

• Do not use as baby wipes.

• Do not use in or contact the eyes.

Avoid contact with open or exposed wounds

When Using

Keep out of eyes, ears, and mouth.

In case of contact with eyes, rinse eyes thoroughly with water

Stop Use

Stop use if too much skin irritation and sensitivity develops or increases

Keep out of reach of children. If swallowed, get medical help or contact a Poison Control Center immediately.

Directions

• Open lid, gently peel back resealable label, remove and use wipes as required

• Reseal after use to avoid evaporation of alcohol it is a violation of federal law to use this product in a manner inconsistent with its labeling.

Other Informations

• Store at room temperature 15-30°C (59-86°F).

• Lot No. Manufacture date and expiration date can be found on package.

Inactive Ingredients

Aqua, Olus Oil, Glycerin, Lauryl Glucoside, Polyglyceryl-2- Dipolihydroxystearate, Glyceryl Oleate, Dicapyryl Carbonate, Perfume, Triethanolamine

ANTIBACTERIAL

ANTI-FUNGAL

Kills 99.9% Bacteria & Germs

pH 5.5

BLEACH FREE

Distributed by IVI

200 Blydenburg Rd.

Unit 3 - Islandia NY 11749

Email:info@drclinicusa.com

Phone: (800)686-5044